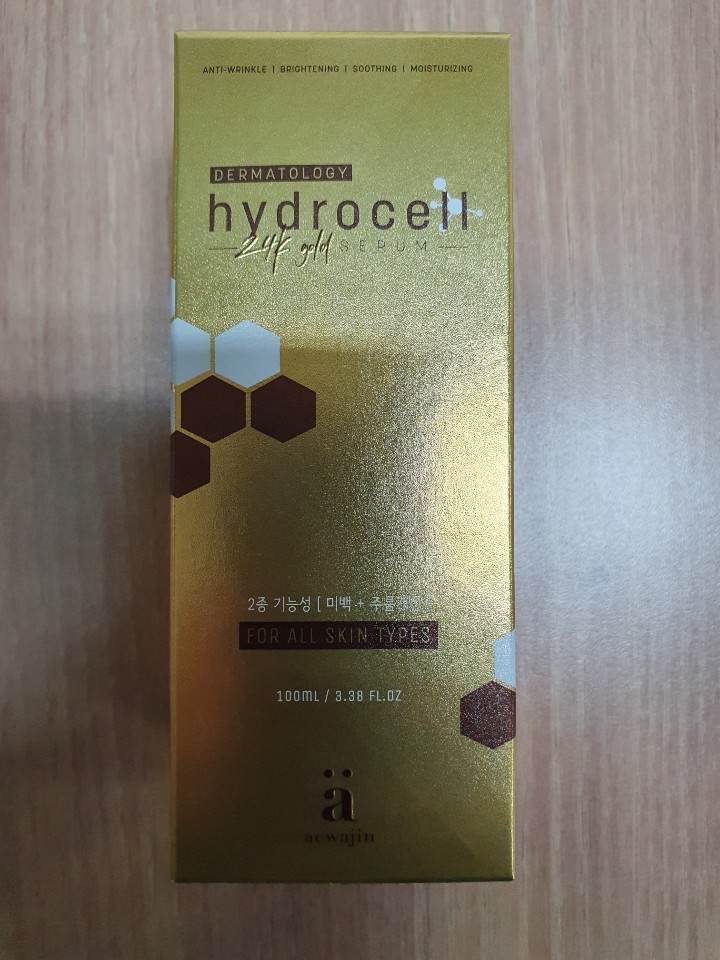 DRUG LABEL: aewajin Derma Hydrocell 24k Gold Serum
NDC: 73466-0005 | Form: LIQUID
Manufacturer: MISOCOS
Category: otc | Type: HUMAN OTC DRUG LABEL
Date: 20240705

ACTIVE INGREDIENTS: GLYCERIN 5 g/100 mL
INACTIVE INGREDIENTS: WATER; ALLANTOIN

Drug Facts

ACTIVE INGREDIENT

glycerin

INACTIVE INGREDIENT

Water
Butylene Glycol
Sodium Hyaluronate
Glycerin
Propylene Glycol
Niacinamide
Trehalose
Betaine
Polysorbate 80
PEG/PPG-17/6 Copolymer
Disodium EDTA
GOLD
Fragrance
Triethanolamine
Chlorphenesin
Phenoxyethanol
Adenosine
Chrysanthemum Indicum Callus Culture Extract
Anthemis Nobilis Flower Extract
Centella Asiatica Extract
Allantoin
Hamamelis Virginiana Extract
Aloe Barbadensis Leaf Extract
Rosa Centifolia Flower Extract
Galactomyces Ferment Filtrate
Bifida Ferment Extract

PURPOSE

skin protectant

keep out of reach of the children

INDICATIONS AND USAGE

take a suitable amount on the skin

WARNINGS

■ if following abnormal symptoms occurs after use , stop use and consult with a skin specialist

red specks, swelling, itching

■ don’t use on the part where there is injury, eczema, or dermatitis

Keep out of reach of children

■ if swallowed, get medical help or contact a person control center immediately

DOSAGE AND ADMINISTRATION

for external use only